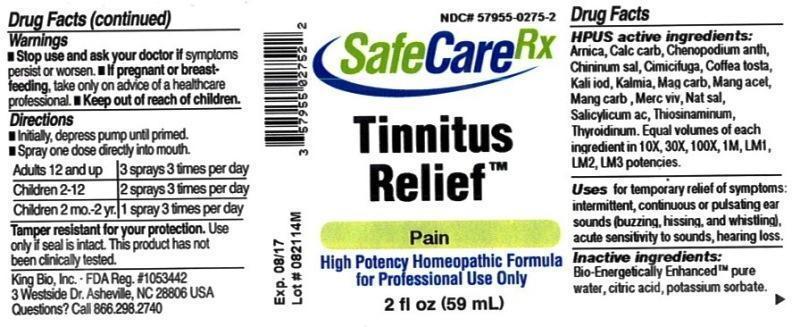 DRUG LABEL: Tinnitus Relief
NDC: 57955-0275 | Form: LIQUID
Manufacturer: King Bio Inc.
Category: homeopathic | Type: HUMAN OTC DRUG LABEL
Date: 20150304

ACTIVE INGREDIENTS: ARNICA MONTANA 10 [hp_X]/59 mL; OYSTER SHELL CALCIUM CARBONATE, CRUDE 10 [hp_X]/59 mL; DYSPHANIA AMBROSIOIDES 10 [hp_X]/59 mL; QUININE SALICYLATE 10 [hp_X]/59 mL; BLACK COHOSH 10 [hp_X]/59 mL; COFFEA ARABICA SEED, ROASTED 10 [hp_X]/59 mL; POTASSIUM IODIDE 10 [hp_X]/59 mL; KALMIA LATIFOLIA LEAF 10 [hp_X]/59 mL; MAGNESIUM CARBONATE 10 [hp_X]/59 mL; MANGANESE ACETATE TETRAHYDRATE 10 [hp_X]/59 mL; MANGANESE CARBONATE 10 [hp_X]/59 mL; MERCURY 10 [hp_X]/59 mL; SODIUM SALICYLATE 10 [hp_X]/59 mL; SALICYLIC ACID 10 [hp_X]/59 mL; ALLYLTHIOUREA 10 [hp_X]/59 mL; THYROID, UNSPECIFIED 10 [hp_X]/59 mL
INACTIVE INGREDIENTS: WATER; ANHYDROUS CITRIC ACID; POTASSIUM SORBATE

Tinnitus Relief™

ACTIVE INGREDIENT

Drug Facts__________________________________________________________________________________________________________

HPUS active ingredients: Arnica montana, Calcarea carbonica, Chenopodium anthelminticum, Chininum salicylicum, Cimicifuga racemosa, Coffea tosta, Kali iodatum, Kalmia latifolia, Magnesia carbonica, Manganum acxeticum, Manganum carbonicum, Mercurius vivus, Natrum salicylicum, Salicylicum acidum, Thiosinaminum, Thyroidinum. Equal volumes of each ingredient in 10X, 30X, 100X, 1M, LM1, LM2, LM3 potencies.

INDICATIONS AND USAGE

Uses for temporary relief of symptoms: intermittent, continuous or pulsating ear sounds (buzzing, hissing, and whistling), acute sensitivity to sounds, hearing loss.

Inactive Ingredients:

Bio-Energetically Enhanced™ pure water, citric acid and potassium sorbate.

Warnings

- Stop use and ask your doctor if symptoms persist or worsen.
- If pregnant or breast-feeding, take only on advice of a healthcare professional.

- Keep out of reach of children.

Directions

- Initially, depress pump until primed.
- Spray one dose directly into mouth.
- Adults 12 and up: 3 sprays 3 times per day
- Children 2-12: 2 sprays 3 times per day
- Children 2mo-2yr.: 1 spray 3 times per day

OTHER SAFETY INFORMATION

Tamper resistant for your protection. Use only if safety seal is intact. This product has not been clinically tested.

PURPOSE

Uses for temporary relief of symptoms:

- intermittent, continuous or pulsating ear sounds (buzzing, hissing, and whistling)
- acute sensitivity to sounds
- hearing loss.